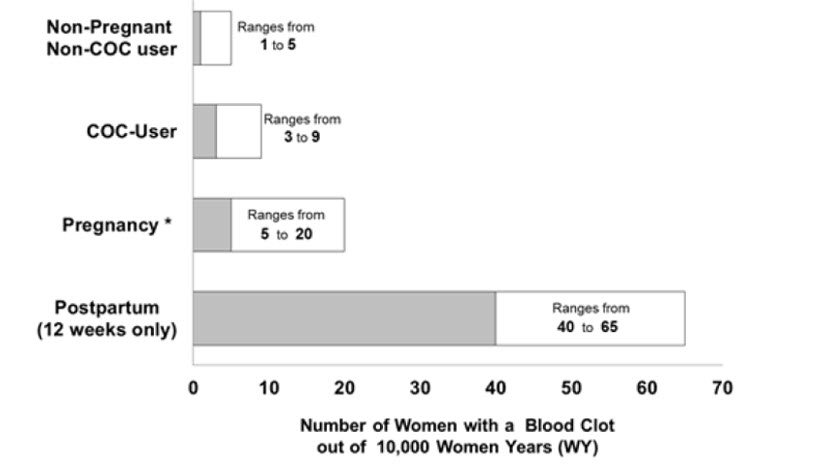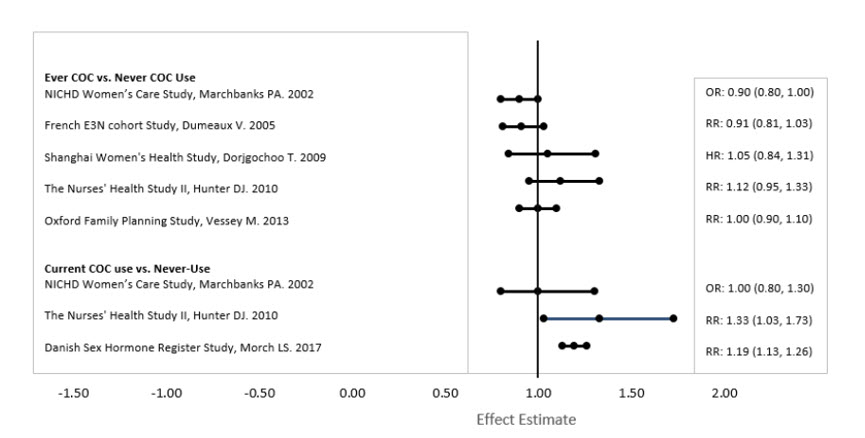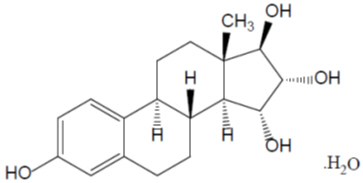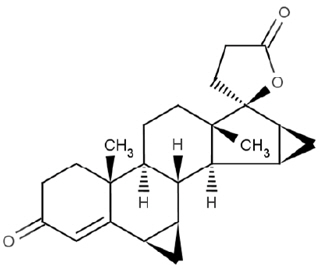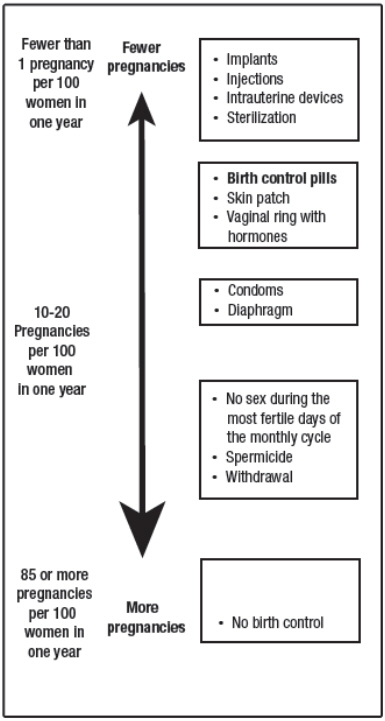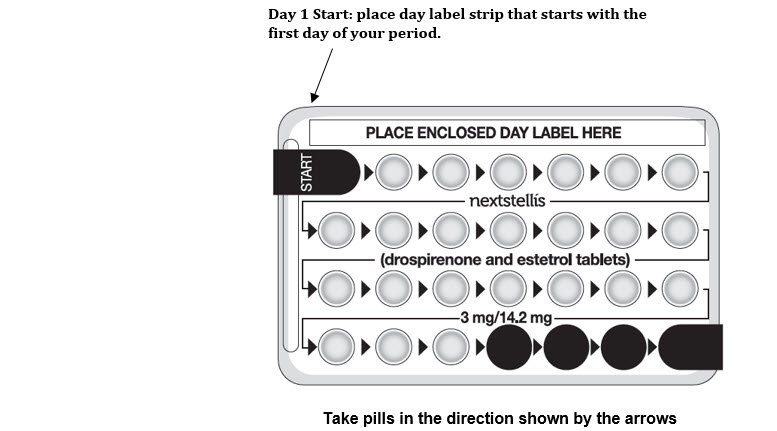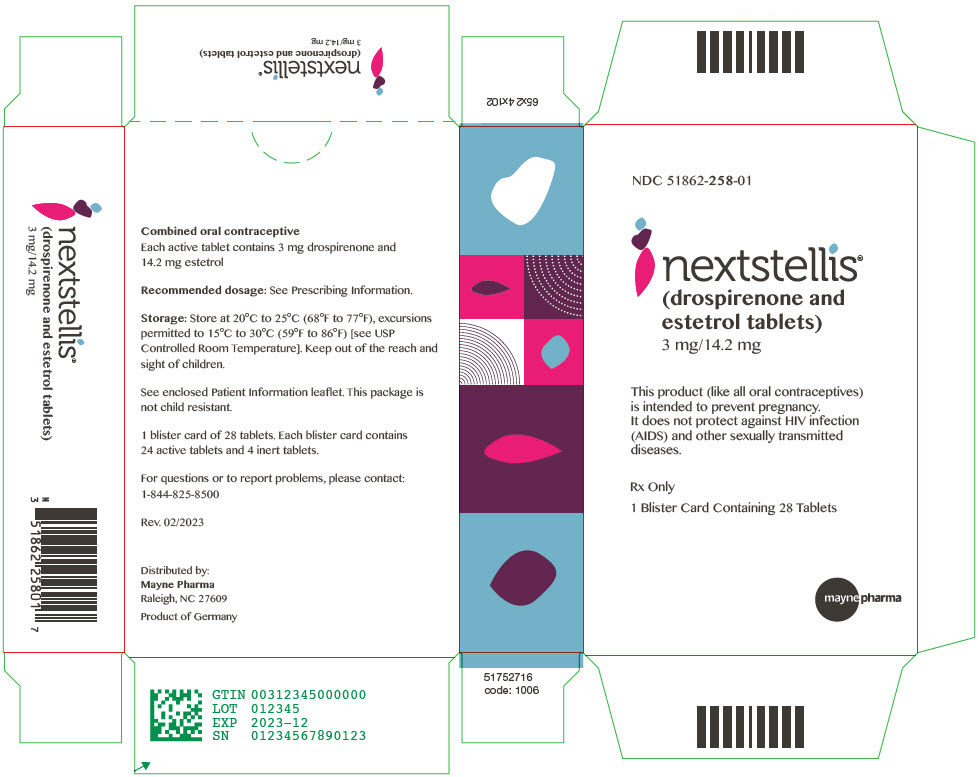 DRUG LABEL: Nextstellis
NDC: 51862-258 | Form: KIT | Route: ORAL
Manufacturer: Mayne Pharma
Category: prescription | Type: HUMAN PRESCRIPTION DRUG LABEL
Date: 20230511

ACTIVE INGREDIENTS: drospirenone 3 mg/1 1; estetrol monohydrate 14.2 mg/1 1
INACTIVE INGREDIENTS: lactose monohydrate; sodium starch glycolate type A; starch, corn; povidone k30; magnesium stearate; hypromellose, unspecified; hydroxypropyl cellulose, unspecified; talc; hydrogenated cottonseed oil; titanium dioxide; ferric oxide red; lactose monohydrate; starch, corn; magnesium stearate; hypromellose, unspecified; hydroxypropyl cellulose, unspecified; talc; hydrogenated cottonseed oil; titanium dioxide

HIGHLIGHTS OF PRESCRIBING INFORMATION

These highlights do not include all the information needed to use NEXTSTELLIS safely and effectively. See full prescribing information for NEXTSTELLIS.
NEXTSTELLIS® (drospirenone and estetrol tablets), for oral use
Initial U.S. Approval: 2021

WARNING: CIGARETTE SMOKING AND SERIOUS CARDIOVASCULAR EVENTS

See full prescribing information for complete boxed warning.

- Females over 35 years old who smoke should not use NEXTSTELLIS (4)
- Cigarette smoking increases the risk of serious cardiovascular events from combination oral contraceptive (COC) use. (4)

RECENT MAJOR CHANGES

Warnings and Precautions (5.5) | 04/2022

1 INDICATIONS AND USAGE

NEXTSTELLIS is a combination of drospirenone, a progestin, and estetrol, an estrogen, indicated for use by females of reproductive potential to prevent pregnancy. (1)

Limitations of Use

NEXTSTELLIS may be less effective in females with a BMI ≥ 30 kg/m^2. In females with BMI ≥ 30 kg/m^2, decreasing effectiveness may be associated with increasing BMI (14).

2 DOSAGE AND ADMINISTRATION

- Take one tablet by mouth at the same time every day. (2.1)
- Take tablets in the order directed on the blister pack. (2.1)

3 DOSAGE FORMS AND STRENGTHS

NEXTSTELLIS consists of 28 tablets in the following order (3):

- 24 pink active tablets each containing drospirenone 3 mg and estetrol 14.2 mg
- 4 white inert tablets

4 CONTRAINDICATIONS

- A high risk of arterial or venous thrombotic diseases (4)
- Breast cancer or history of breast cancer (4)
- Hepatic adenoma, hepatocellular carcinoma, acute hepatitis or decompensated cirrhosis (4)
- Co-administration with hepatitis C drug combinations containing ombitasvir/paritaprevir/ritonavir, with or without dasabuvir (4, 7.1)
- Abnormal uterine bleeding that has an undiagnosed etiology (4)
- Renal impairment (4)
- Adrenal insufficiency (4)

5 WARNINGS AND PRECAUTIONS

- Thromboembolic Disorders and Other Vascular Problems: Stop NEXTSTELLIS if a thrombotic or thromboembolic event occurs. Start no earlier than 4 weeks after delivery. Consider all cardiovascular risk factors before initiating in any female, particularly in the presence of multiple risk factors. (5.1)
- Hyperkalemia: Check serum potassium concentration during the first NEXTSTELLIS treatment cycle in females on long-term treatment with medications that may increase serum potassium concentration. (5.2, 7.2)
- Hypertension: Monitor blood pressure periodically and stop use if blood pressure rises significantly. (5.3)
- Migraine: Discontinue if new, recurrent, persistent, or severe migraines occur. (5.4)
- Hormonally-Sensitive Malignancy: Discontinue NEXTSTELLIS if a hormonally-sensitive malignancy is diagnosed. (5.5)
- Liver Disease: Withhold or permanently discontinue for persistent or significant elevation of liver enzymes. (5.6)
- Glucose Tolerance and Hypertriglyceridemia: Monitor glucose in females with prediabetes or diabetes. Consider an alternate contraceptive method for females with hypertriglyceridemia. (5.8)
- Gallbladder Disease and Cholestasis: Consider discontinuing NEXTSTELLIS in females with symptomatic gallbladder or cholestatic disease. (5.9)
- Bleeding Irregularities and Amenorrhea: May cause irregular bleeding or amenorrhea. Evaluate for other causes if symptoms persist. (5.11)

6 ADVERSE REACTIONS

Most common adverse reactions (≥2%): bleeding irregularities, mood disturbance, headache, breast symptoms, dysmenorrhea, acne, weight increased, and libido decreased (6)

To report SUSPECTED ADVERSE REACTIONS, contact Mayne Pharma at 1-844-825-8500 or FDA at 1-800-FDA-1088 or www.fda.gov/medwatch

7 DRUG INTERACTIONS

- CYP3A Inducers: May lead to contraceptive failure and/or increase breakthrough bleeding. Avoid concomitant use. If concomitant use is unavoidable, use an alternative or back-up contraceptive method during co-administration and up to 28 days after discontinuation of the CYP3A inducer. (7.1)
- See Full Prescribing Information for additional clinically significant drug interactions (7).

8 USE IN SPECIFIC POPULATIONS

- Pregnancy: Discontinue if pregnancy occurs. (8.1)
- Lactation: Advise postpartum females that NEXTSTELLIS can decrease milk production. (8.2)

FULL PRESCRIBING INFORMATION

WARNING: CIGARETTE SMOKING AND SERIOUS CARDIOVASCULAR EVENTS

Cigarette smoking increases the risk of serious cardiovascular events from combined hormonal contraceptive (CHC) use. This risk increases with age, particularly in females over 35 years of age, and with the number of cigarettes smoked. For this reason, CHCs, including NEXTSTELLIS, are contraindicated in females who are over 35 years of age and smoke. [See Contraindications (4) and Warnings and Precautions (5.1)]

1 INDICATIONS AND USAGE

NEXTSTELLIS is indicated for use by females of reproductive potential to prevent pregnancy.

Limitations of Use

NEXTSTELLIS may be less effective in females with a BMI ≥ 30 kg/m^2. In females with BMI ≥ 30 kg/m^2, decreasing effectiveness may be associated with increasing BMI [see Clinical Studies (14)].

2 DOSAGE AND ADMINISTRATION

2.1 Recommended Dosage and Administration

Start NEXTSTELLIS using a Day 1 start. Take one tablet by mouth at the same time every day with or without food.

2.2 Additional Administration Information

To achieve maximum contraceptive effectiveness, take one tablet every day at about the same time each day. The recommended dosage of NEXTSTELLIS is one tablet daily for 28 consecutive days: one pink active tablet daily during the first 24 days followed by one white inactive tablet daily during the 4 following days (see Table 1).

Table 1 NEXTSTELLIS Administration Instructions
Starting NEXTSTELLIS in females with no current use of hormonal contraception | Important:; - In females with irregular menstrual cycles, pregnancy testing may be necessary prior to initiation of this product.; Day 1 Start:; - Take the first pink active tablet on the first day of menses. - Take subsequent pink active tablets once daily at the same time each day for a total of 24 days. - Take one white inert tablet daily for 4 days and at the same time of day that active tablets were taken. - Begin each subsequent 28-day pack on the same day of the week as the first cycle pack (i.e., on the day after taking the last tablet); If not starting on the first day of menses, use a non-hormonal contraceptive (e.g. condoms and/or spermicide) as back-up until one active tablet has been taken daily for 7 days in a row.
Switching to NEXTSTELLIS from another contraceptive method | Start NEXTSTELLIS on the day:
- Combined Oral Contraceptive (COC) | - When the new pack of the previous COC would have started.
- Transdermal System | - When the next application would have been scheduled.
- Vaginal Insert | - When the next insertion would have been scheduled.
- Injection | - When the next injection would have been scheduled.
- Intrauterine System (IUS) | - After removal.
- Implant | - After removal.
- Progestin-only pill | - After the last tablet was taken.
Starting NEXTSTELLIS after delivery (>20 weeks gestation) | Must not start earlier than 4 weeks after delivery (due to the increased risk of thromboembolism [see Contraindications (4) and Warnings and Precautions (5.1)] If menstrual cycles have returned, follow instructions for "Starting NEXTSTELLIS in females with no current use of hormonal contraception". If menstrual cycles have not resumed, consider the possibility of ovulation and pregnancy. If not pregnant, use additional nonhormonal contraception for the first 7 days of NEXTSTELLIS use.
Starting NEXTSTELLIS after Abortion or Miscarriage; - ≤14 weeks gestation | Within the first 7 days of complete first trimester abortion or miscarriage, use additional nonhormonal contraception for the next 7 days. After the first 7 days, follow instructions for "Starting NEXTSTELLIS in females with no current use of hormonal contraception".
- > 14 weeks but ≤ 20 weeks gestation | After 4 weeks following second trimester abortion or miscarriage. Consider duration of pregnancy and increased risk of thromboembolism [see Warnings and Precautions (5.1)] If menstrual cycles have returned, follow instructions for "Starting NEXTSTELLIS in females with no current use of hormonal contraception." If menstrual cycles have not resumed, consider the possibility of ovulation and pregnancy. If not pregnant, use additional nonhormonal contraception for the first 7 days of NEXTSTELLIS use.

2.3 Missed Doses

Table 2 Instructions for Missed NEXTSTELLLIS Tablets in a Monthly Dosing Regimen
- If one pink active tablet is missed | Take the missed tablet as soon as possible and take the next tablet at the scheduled time, even if two active tablets are taken in one day. Continue taking one tablet a day until the pack is finished.
- If two or more pink active tablets are missed in Week 1 or Week 2 | Take one missed tablet as soon as possible and take the tablet for the current day (that means taking two tablets in one day) and discard the other missed tablets. Continue taking one tablet a day until the pack is finished. Use additional non-hormonal contraception as back-up until pink tablets have been taken for 7 consecutive days.
- If two pink active tablets are missed in Week 3 | Take one missed tablet as soon as possible and take the tablet for the current day (that means taking two tablets in one day) and discard the other missed tablets. Finish the active tablets and discard the inactive tablets in the pack. Start a new pack of tablets the next day. Use additional non-hormonal contraception as back-up until pink tablets have been taken for 7 consecutive days.
- If one or more white inert tablets are missed | Skip the missed pill days and continue taking one tablet a day until the pack is finished.

2.4 Administration Recommendations after Vomiting or Acute Diarrhea

If vomiting or acute diarrhea occurs within 3 to 4 hours after taking an active tablet, take the new active tablet (scheduled for the next day) as soon as possible. Take the new tablet within 12 hours of the usual time of tablet-taking if possible. If more than two tablets are missed, follow the advice concerning missed tablets, including using backup non-hormonal contraception. For additional recommendations, refer to the table above [see Dosage and Administration (2.3)].

3 DOSAGE FORMS AND STRENGTHS

NEXTSTELLIS (drospirenone and estetrol tablets) is available in a blister card, with 28 6-mm round, bi-convex film-coated tablets in the following order:

- 24 pink active tablets containing 3 mg drospirenone and 14.2 mg estetrol embossed with a drop-shaped logo on one side.
- 4 white inert tablets embossed with a drop-shaped logo on one side.

4 CONTRAINDICATIONS

NEXTSTELLIS is contraindicated in females who are known to have or develop the following conditions:

- A history of, increased risk for, or current arterial or venous thrombotic/thromboembolic diseases. Examples include females who are known to:
  - Smoke, if 35 years of age and older [see Boxed Warning and Warnings and Precautions (5.1)]
  - Have current or history of deep vein thrombosis or pulmonary embolism [see Warnings and Precautions (5.1)]
  - Have cerebrovascular disease [see Warnings and Precautions (5.1)]
  - Have coronary artery disease [see Warnings and Precautions (5.1)]
  - Have thrombogenic valvular or thrombogenic rhythm diseases of the heart (for example, subacute bacterial endocarditis with valvular disease, or atrial fibrillation) [see Warnings and Precautions (5.1)]
  - Have inherited or acquired hypercoagulopathies [see Warnings and Precautions (5.1)]
  - Have uncontrolled hypertension or hypertension with vascular disease [see Warnings and Precautions (5.1)]
  - Have diabetes mellitus with hypertension or end-organ damage; or diabetes mellitus of > 20 years duration [see Warnings and Precautions (5.9)]
  - Have migraine headaches with aura [see Warnings and Precautions (5.4)]
- Current diagnosis of, or history of, breast cancer, which may be hormone-sensitive [see Warnings and Precautions (5.5)]
- Hepatic adenoma, hepatocellular carcinoma, acute hepatitis, or severe (decompensated) cirrhosis [see Warnings and Precautions (5.6)]
- Use of hepatitis C drug combinations containing ombitasvir/paritaprevir/ritonavir, with or without dasabuvir, due to the potential for ALT elevations [see Warnings and Precautions (5.7)]
- Abnormal uterine bleeding that has an undiagnosed etiology [see Warnings and Precautions (5.5)]
- Renal Impairment [see Warnings and Precautions (5.2)]
- Adrenal insufficiency [see Warnings and Precautions (5.2)]

5 WARNINGS AND PRECAUTIONS

5.1 Thromboembolic Disorders and Other Vascular Problems

- Stop NEXTSTELLIS if an arterial or venous thrombotic/thromboembolic event occurs.
- Stop NEXTSTELLIS if there is unexplained loss of vision, proptosis, diplopia, papilledema, or retinal vascular lesions and evaluate for retinal vein thrombosis immediately.
- Discontinue NEXTSTELLIS during prolonged immobilization.
- Start NEXTSTELLIS no earlier than four weeks after delivery in females who are not breast feeding. The risk of postpartum thromboembolism decreases after the third postpartum week, whereas the likelihood of ovulation increases after the third postpartum week.

Before starting NEXTSTELLIS, evaluate any past medical history or family history of thrombotic or thromboembolic disorders and consider whether the history suggests an inherited or acquired hypercoagulopathy. NEXTSTELLIS is contraindicated in females with a high risk of arterial or venous thrombotic/thromboembolic diseases [see Contraindications (4)].

Cardiovascular and Cerebrovascular Events

Use of CHCs increases the risk of cardiovascular events and cerebrovascular events, such as myocardial infarction and stroke. The risk is greater among females over age 40, smokers, and females with hypertension, dyslipidemia, diabetes, or obesity. The risk increases with age, particularly in females 35 years of age and older, and with the number of cigarettes smoked. In addition to cigarettes, use of other nicotine-containing products – including cigars, smokeless tobacco, hookah tobacco, e-cigarettes, and nicotine replacement therapy – may also increase the risk of serious cardiovascular events from CHC use.

Venous Thromboembolism

Use of CHCs also increases the risk of venous thromboembolic events (VTEs), such as deep vein thrombosis and pulmonary embolism. The rate of VTE in females using COCs has been estimated to be 3 to 9 cases per 10,000 woman-years and should be considered in the context of other female of reproductive potential subpopulations who are not taking CHCs [see Adverse Reactions (6.1)].

Risk factors for VTEs include smoking, obesity, family history of VTE, and prolonged immobilization in addition to other factors that contraindicate use of CHCs [see Contraindications (4)]. The presence of multiple risk factors for VTE may increase the risk synergistically. The risk of VTE is highest during the first year of CHC use and when restarting hormonal contraception after a break of four weeks or longer. The risk of VTE returns to baseline approximately 3 months after CHC use is discontinued.

Postpartum Venous Thromboembolism

The risk of VTE is increased during the first six weeks postpartum compared to the risk in non-pregnant, non-postpartum females. The risk is highest in the first three weeks postpartum, but remains higher than baseline until at least six weeks postpartum. The presence of multiple risk factors for VTE may further increase the risk. Obstetric complications may extend the elevated risk up to 12 weeks postpartum.

Figure 1 shows the risk of developing a VTE for females who are not pregnant and do not use COCs, for females who use COCs, for pregnant females, and for females in the postpartum period. To put the risk of developing a VTE into perspective: if 10,000 females who are not pregnant and do not use oral contraceptives are followed for one year, between 1 and 5 of these females will develop a VTE.

Figure 1 Likelihood of Developing a VTE

Two prospective studies of NEXTSTELLIS have been conducted, one in Europe/Russia (NCT02817828; C301) and one in North America (NCT02817841; C302) (N=3,632), for the prevention of pregnancy in females 16-50 years of age. There was one reported VTE in the Europe/Russia study [see Adverse Reactions (6.1)].

5.2 Hyperkalemia

NEXTSTELLIS is contraindicated in females with conditions that predispose to hyperkalemia (e.g., renal impairment, hepatic impairment, and adrenal insufficiency). Females receiving daily, long-term treatment for chronic conditions or diseases with medications that may increase serum potassium concentration should have their serum potassium concentration checked during the first treatment cycle. Monitor serum potassium concentration in females at increased risk for hyperkalemia (i.e., those females who take a strong CYP3A4 inhibitor long-term and concomitantly with NEXTSTELLIS). [see Drug interactions (7)]. Monitor females taking NEXTSTELLIS who later develop medical conditions and/or begin medication that put them at an increased risk for hyperkalemia.

NEXTSTELLIS contains drospirenone, a progestin, which has anti-mineralocorticoid activity, including the potential for hyperkalemia in high-risk females, comparable to a 25 mg dose of spironolactone. In two Phase 3 trials of NEXTSTELLIS (N = 3,632) for the prevention of pregnancy in females 16-50 years of age, seven subjects were noted to have hyperkalemia and one subject discontinued due to elevated potassium levels. Most females who developed hyperkalemia in the clinical development studies of NEXTSTELLIS had only mild potassium elevations and/or isolated increases that returned to normal while still on study medication.

5.3 Hypertension

NEXTSTELLIS is contraindicated in females with uncontrolled hypertension or hypertension with vascular disease [see Contraindications (4)]. For all females, including those with well-controlled hypertension, monitor blood pressure periodically and stop NEXTSTELLIS if blood pressure rises significantly.

An increase in blood pressure has been reported in females using COCs. This increase is more likely in older females with extended duration of use.

5.4 Migraine

NEXTSTELLIS is contraindicated in females who have migraines with aura [see Contraindications (4)]. Discontinue NEXTSTELLIS in females using NEXTSTELLIS who develop new migraines that are recurrent, persistent, or severe. Discontinue NEXTSTELLIS if there is an increased frequency or severity of migraines during CHC use (which may be prodromal of a cerebrovascular event).

Migraines with aura increase the risk for stroke. This stroke risk is further increased in females who have migraines with aura with use of CHCs.

5.5 Malignant Neoplasms

Breast Cancer

NEXTSTELLIS is contraindicated in females who currently have or have had breast cancer because breast cancer may be hormonally sensitive [see Contraindications (4)].

Epidemiology studies have not found a consistent association between use of combined oral contraceptives (COCs) and breast cancer risk. Studies do not show an association between ever (current or past) use of COCs and risk of breast cancer. However, some studies report a small increase in the risk of breast cancer among current or recent users (<6 months since last use) and current users with longer duration of COC use [see Postmarketing Experience (6.2)].

Cervical Cancer

A causal relationship between the use of CHCs and the development of cervical cancer and intraepithelial neoplasia has not been clearly established. In observational studies, the use of oral hormonal contraceptives in females for five years or more, compared to females who did not use oral hormonal contraceptives, was associated with an increased risk of cervical cancer and intraepithelial neoplasia. In these studies, the use of oral hormonal contraceptives in females for 10 years or more, compared to females who received oral hormonal contraceptives for 5-9 years, was associated with an increased risk of cervical cancer and intraepithelial neoplasia. Limitations in these epidemiologic studies include potential recall bias, differences in sexual behavior, and other factors such as establishing whether there were data on persistent high-risk Human Papilloma Virus (HPV) infection.

5.6 Liver Disease

Elevated Liver Enzymes

NEXTSTELLIS is contraindicated in females with acute hepatitis or severe (decompensated) cirrhosis [see Contraindications (4)]. Withhold or permanently discontinue NEXTSTELLIS for persistent or significant elevation of liver enzymes. NEXTSTELLIS can cause elevated liver enzymes.

Liver Tumors

NEXTSTELLIS is contraindicated in females with hepatic adenomas and malignant liver tumors [see Contraindications (4)]. CHCs increase the risk of hepatic tumors, particularly hepatic adenomas. Rupture of hepatic adenomas may cause death from abdominal hemorrhage.

5.7 Risk of Liver Enzyme Elevations with Concomitant Hepatitis C Treatment

CHCs, such as NEXTSTELLIS, are contraindicated for use with Hepatitis C drug combinations containing ombitasvir/paritaprevir/ritonavir (with or without dasabuvir) [see Contraindications (4)]. Discontinue NEXTSTELLIS prior to starting therapy with the combination drug regimen ombitasvir/paritaprevir/ritonavir (with or without dasabuvir). NEXTSTELLIS can be restarted approximately 2 weeks following completion of treatment with this hepatitis C combination drug regimen.

During clinical trials with the above-mentioned Hepatitis C combination drug regimen, ALT elevations greater than 5 times the upper limit of normal (ULN), including some cases greater than 20 times the ULN, were significantly more frequent in females using ethinyl estradiol (EE)-containing drugs, such as CHCs. Females using medications containing estrogens other than EE had a rate of ALT elevation similar to those not receiving any estrogens. NEXTSTELLIS contains E4 rather than EE, but as no data are available for co-administration with this Hepatitis C combination drug regimen, caution is warranted.

5.8 Glucose Tolerance and Hypertriglyceridemia

Glucose Tolerance

Carefully monitor females with prediabetes and diabetes who are using NEXSTELLIS. NEXTSTELLIS may decrease glucose tolerance [see Clinical Pharmacology (12.2)].

Hypertriglyceridemia

Consider alternative contraception for females with hypertriglyceridemia. Females with hypertriglyceridemia, or a family history thereof, may have an increase in serum triglyceride concentrations when using NEXSTELLIS, which may increase the risk of pancreatitis.

5.9 Gallbladder Disease and Cholestasis

Consider discontinuing NEXTSTELLIS in females with symptomatic gallbladder disease or cholestatic disease. Studies suggest an increased risk of developing gallbladder disease among CHC users. Use of CHCs may also worsen existing gallbladder disease.

A past history of CHC-related cholestasis predicts an increased risk with subsequent CHC use. Females with a history of pregnancy-related cholestasis may be at an increased risk for CHC-related cholestasis.

5.10 Effect on Binding Globulins

Increase the dosage of thyroid hormone replacement therapy as needed in females taking NEXTSTELLIS [see Clinical Pharmacology (12.2)]. The estrogen component of NEXTSTELLIS may increase the serum concentrations of thyroxine-binding globulin, sex hormone-binding globulin, and cortisol-binding globulin.

5.11 Bleeding Irregularities and Amenorrhea

Unscheduled Bleeding and Spotting

Females using NEXTSTELLIS may experience unscheduled (breakthrough or intracyclic) bleeding and spotting, especially during the first 4 months of use. Bleeding irregularities may resolve over time or by changing to a different contraceptive product. If bleeding persists or occurs after previously regular cycles, evaluate for causes such as pregnancy or malignancy.

Unscheduled bleeding was defined as bleeding or spotting that occurred on Day 4 through Day 24 of a 28-day cycle. Based on subject diaries from C302 (US/CA), the proportion of subjects reporting unscheduled bleeding or spotting per 28-day cycle decreased over time: 30.3% at Cycle 1 versus 17.4% at Cycle 12. The mean number of unscheduled bleeding/spotting days per cycle also gradually decreased over time, with a mean of 0.4 (± 1.42) bleeding days at Cycle 1, versus a mean of 0.2 (± 0.98) bleeding days at Cycle 12.

Absence of Scheduled Bleeding

Females who use NEXTSTELLIS may experience absence of scheduled (withdrawal) bleeding, even if they are not pregnant [See Adverse Reactions (6)]. The proportion of subjects reporting absence of scheduled bleeding remained constant overall, with on average 15.5% of subjects reporting absence of scheduled bleeding from Cycles 1 through 12.

If scheduled bleeding does not occur, consider the possibility of pregnancy. If the patient has not adhered to the prescribed dosing schedule (missed one or two active tablets or started taking them on a day later than prescribed), consider the possibility of pregnancy at the time of the first missed period and perform appropriate diagnostic measures.

After discontinuation of NEXTSTELLIS, amenorrhea or oligomenorrhea may occur, especially if these conditions were pre-existent.

5.12 Depression

Monitor females with a history of depression and discontinue NEXTSTELLIS if depression recurs to a serious degree. Data on the association of COCs with onset of depression or exacerbation of existing depression are limited.

5.13 Hereditary Angioedema

Avoid NEXTSTELLIS in females with hereditary angioedema. Exogenous estrogens may induce or exacerbate symptoms of hereditary angioedema.

5.14 Chloasma

Avoid NEXTSTELLIS in females with a history of chloasma gravidarum or increased sensitivity to sun and/or ultraviolet radiation exposure. Chloasma may occur with NEXTSTELLIS use, especially in females with a history of chloasma gravidarum.

6 ADVERSE REACTIONS

The following clinically significant adverse reactions with the use of COCs are discussed elsewhere in labeling:

- Serious cardiovascular events including venous and arterial thromboembolism [see Boxed Warning and Warnings and Precautions (5.1)]
- Hyperkalemia [see Warnings and Precautions (5.2)]
- Liver disease [see Warnings and Precautions (5.5)]

6.1 Clinical Trials Experience

Because clinical trials are conducted under widely varying conditions, adverse reaction rates observed in the clinical trials of one drug cannot be directly compared to rates in the clinical trials of another drug and may not reflect the rates observed in practice.

The data provided reflect the experience with the use of NEXTSTELLIS in two large prospective studies, one in Europe/Russia (C301) and one in North America (C302) (N = 3,632) of NEXTSTELLIS for the prevention of pregnancy in females 16-50 years of age. The mean duration of NEXTSTELLIS exposure was 317 and 257 days for the respective studies. The study population was 27 years of age on average, with a mean BMI of 25 kg/m^2. The racial distribution was 83% White; 11% Black; 3% Asian; and 3% Other.

Table 4 Adverse Reactions Occurring in ≥ 2% of Females Receiving NEXTSTELLIS in Studies C301 and C302
Preferred Term (PT) | Participants with Adverse Reaction – US/Canada Phase 3 trial (n [%]) (N = 2073) [Represents the safety population of C302 only (US/Canada).] | Participants with Adverse Reaction – Two Phase 3 trials (n [%]) (N=3632) [Represents the safety population of C301/C302 for DRSP/E4.]
Any adverse reaction [Any adverse reaction equals any adverse event ≥ 2%.] | 1205 (58.1) | 2126 (58.5)
Mood disturbance [Includes PTs: adjustment disorder, affective disorder, agitation, anger, anxiety, depressed mood, depression, depressive symptom, disorientation, emotional disorder, emotional distress, euphoric mood, generalized anxiety disorder, insomnia, irritability, mood altered, mood swings, nervousness, panic attack, panic disorder, performance fear, restlessness, sleep disorder, stress, suicidal ideation, tearfulness.] | 226 (10.9) | 329 (9.1)
Bleeding irregularities [Includes PTs: abnormal withdrawal bleeding, amenorrhea, cervix hemorrhage uterine, coital bleeding, dysfunctional uterine bleeding, menometrorrhagia, menorrhagia, menstrual disorder, menstruation irregular, metrorrhagia, oligomenorrhea, polymenorrhea, uterine hemorrhage, vaginal hemorrhage.] | 201 (9.7) | 393 (10.8)
Breast symptoms [Includes PTs: anisomastia, breast cyst, breast discoloration, breast discomfort, breast disorder, breast engorgement, breast enlargement, breast mass, breast edema, breast pain, breast swelling, breast tenderness, fibrocystic breast disease, galactorrhea, gynecomastia, mastoptosis, nipple disorder, nipple pain.] | 110 (5.3) | 197 (5.4)
Headache [Includes PTs: headache, premenstrual headache, and tension headache.] | 100 (4.8) | 227 (6.3)
Dysmenorrhea [Includes PTs: adnexa uteri pain, dysmenorrhea, premenstrual cramps, pelvic discomfort, pelvic pain, uterine spasm.] | 84 (4.1) | 133 (3.7)
Weight increased [Includes PTs: weight increased, weight fluctuation, body mass index increased, weight loss poor, and obesity.] | 68 (3.3) | 108 (3.0)
Acne [Includes PTs: acne and cystic acne.] | 66 (3.2) | 136 (3.7)
Libido decreased/lost [Includes PTs: libido decreased and loss of libido.] | 27 (1.3) | 72 (2.0)

Adverse Reactions Leading to Study Discontinuation (> 1%)

Of 3,632 females in two clinical studies for prevention of pregnancy in females 16-50 years of age, 9.6% discontinued due to an adverse reaction; the most frequent adverse reaction leading to discontinuation was bleeding irregularity (2.8%). Six subjects (0.17%) discontinued study participation due to new onset of migraine with aura; two subjects (0.05%) discontinued due to severe migraine.

Thromboembolic Disorders and Other Vascular Problems

During studies C301 and C302, one thromboembolic event was reported in a female who had been taking NEXTSTELLIS for 75 days and had normal BMI < 25 kg/m^2.

Depression

In Study C302 (US/CA), 36 (1.7%) subjects reported depression while using NEXTSTELLIS. Nine (0.3%) subjects had drug withdrawn as a result of symptoms of depression.

6.2 Postmarketing Experience

Five studies that compared breast cancer risk between ever-users (current or past use) of COCs and never-users of COCs reported no association between ever use of COCs and breast cancer risk, with effect estimates ranging from 0.90 - 1.12 (Figure 2).

Three studies compared breast cancer risk between current or recent COC users (<6 months since last use) and never users of COCs (Figure 2). One of these studies reported no association between breast cancer risk and COC use. The other two studies found an increased relative risk of 1.19 - 1.33 with current or recent use. Both of these studies found an increased risk of breast cancer with current use of longer duration, with relative risks ranging from 1.03 with less than one year of COC use to approximately 1.4 with more than 8-10 years of COC use.

Figure 2 Relevant Studies of Risk of Breast Cancer with Combined Oral Contraceptives

RR = relative risk; OR = odds ratio; HR = hazard ratio. "ever COC" are females with current or past COC use; "never COC use" are females that never used COCs.

7 DRUG INTERACTIONS

7.1 Effects of Other Drugs on Hormonal Contraceptives

Clinically significant drug interactions with other drugs that affect NEXTSTELLIS are presented in Table 5.

Table 5. Clinically Significant Drug Interactions With Other Drugs that Affect NEXTSTELLIS
CYP3A Inducers
Clinical Effect | DRSP is a CYP3A4 substrate. Concomitant use with strong CYP3A inducers or certain moderate or weak CYP3A inducers may decrease DRSP exposure [see Clinical Pharmacology (12.3)], which may lead to contraceptive failure.
Prevention or Management | Strong CYP3A Inducers | Avoid concomitant use. If concomitant use is unavoidable, use an alternative contraceptive method (e.g., intrauterine system) or backup non-hormonal contraceptive method during coadministration and up to 28 days after discontinuation of the strong CYP3A inducer.
Prevention or Management | Moderate and Weak CYP3A Inducers | Use an alternative or backup contraceptive method during coadministration and up to 28 days after discontinuation of the CYP3A inducer, unless the Prescribing Information of the specific moderate or weak CYP3A inducer indicates there is no clinically significant interaction with NEXTSTELLIS.
Strong CYP3A Inhibitors
Clinical Effect | DRSP is a CYP3A4 substrate. Concomitant use with a strong CYP3A inhibitor may increase DRSP exposure [see Clinical Pharmacology (12.3)], which may increase the risk of adverse reactions of NEXTSTELLIS, including hyperkalemia [see Warnings and Precautions (5.2)].
Prevention or Management | Consider monitoring serum potassium concentration in patients who take a strong CYP3A4 inhibitor long-term and concomitantly with NEXTSTELLIS.
Drugs that May Reduce the Absorption of NEXTSTELLIS
Clinical Effect | Concomitant use with drugs such as bile acid sequestrants may decrease the E4 and DRSP exposure, which may lead to contraceptive failure and/or an increase in breakthrough bleeding.
Prevention or Management | Separate time of administration of NEXTSTELLIS and the concomitant drug. Refer to the concomitant drug's Prescribing Information for additional information.

7.2 Effects of NEXTSTELLIS on Other Drugs

Table 6 includes clinically significant drug interactions with NEXTSTELLIS that affect other drugs.

Table 6. Clinically Significant Drug Interactions of NEXTSTELLIS on Other Drugs
Anti-Diabetic Drugs
Clinical Effect | Concomitant use of NEXTSTELLIS may reduce the blood glucose lowering effect of anti-diabetic drugs [see Warnings and Precautions (5.8) and Clinical Pharmacology (12.2).
Prevention or Management | Increase frequency of glucose monitoring and increase anti-diabetic drug dosage, as needed, based on glucose levels.
Drugs that may increase serum potassium concentration
Clinical Effect | There is a potential for an increase in serum potassium concentration in females taking NEXTSTELLIS with other drugs that may increase serum potassium concentration [see Warnings and Precautions (5.2) and Clinical Pharmacology (12.2)].
Prevention or Management | Monitor serum potassium concentration in females at increased risk for hyperkalemia.
Lamotrigine
Clinical Effect | Concomitant use of NEXTSTELLIS may decrease lamotrigine exposure [see Clinical Pharmacology (12.3)], which may reduce efficacy of lamotrigine.
Prevention or Management | Adjust lamotrigine dosage as recommended in its Prescribing Information based on NEXTSTELLIS initiation or discontinuation.
Systemic Corticosteroids
Clinical Effect | Concomitant use of NEXTSTELLIS may increase the exposure of certain systemic corticosteroids, which may increase the risk of corticosteroid-related adverse reactions [see Clinical Pharmacology (12.2).
Prevention or Management | Follow the recommendation for the corticosteroid in accordance with its Prescribing Information. Consider more frequent monitoring for corticosteroid adverse reactions when used concomitantly with NEXTSTELLIS.
Thyroid Hormone Replacement Therapy
Clinical Effect | Concomitant use of NEXTSTELLIS may increase thyroid-binding globulin concentration [see Warnings and Precautions (5.10) and Clinical Pharmacology (12.2)].
Prevention or Management | Monitor thyroid-stimulating hormone (TSH) level and follow the recommendation for thyroid hormone replacement in accordance with its Prescribing Information.

8 USE IN SPECIFIC POPULATIONS

8.1 Pregnancy

Risk Summary

Discontinue NEXTSTELLIS if pregnancy occurs, because there is no reason to use hormonal contraceptives during pregnancy [see Contraindications (4)]. Epidemiologic studies and meta-analyses have not found an increased risk of genital or nongenital birth defects (including cardiac anomalies and limb-reduction defects) following exposure to COCs before conception or during early pregnancy. Reproductive toxicity studies performed with E4 alone have shown expected pharmacologic effects in animals, which are considered consistent with estrogen exposure.

In the U.S. general population, the estimated background risk of major birth defects and miscarriage in clinically recognized pregnancies is 2 to 4 percent and 15 to 20 percent, respectively.

8.2 Lactation

Risk Summary

Contraceptive hormones and/or metabolites are present in human milk. COCs can reduce milk production in breast-feeding females. This reduction can occur at any time but is less likely to occur once breast-feeding is well established. When possible, advise the nursing woman to use other methods of contraception until she discontinues breast-feeding [see also Dosage and Administration (2.1)]. The developmental and health benefits of breast-feeding should be considered along with the mother's clinical need for NEXTSTELLIS and any potential adverse effects on the breast-fed child from NEXTSTELLIS or from the underlying maternal condition.

After oral administration of DRSP 3 mg/EE 30 µg, about 0.02% of the DRSP dose was excreted into the breast milk of postpartum females within 24 hours. This results in a potential maximal daily dose of less than 1 µg DRSP in an infant.

8.4 Pediatric Use

Safety and efficacy of NEXTSTELLIS have been established in females of reproductive potential. The study population of C302 [see Clinical Studies (14)] was in females of reproduction age 16-50 years of age. Use of NEXTSTELLIS before menarche is not indicated.

8.5 Geriatric Use

NEXTSTELLIS has not been studied in postmenopausal females and is not indicated in this population.

8.6 Hepatic Impairment

NEXTSTELLIS is contraindicated in females with hepatic impairment [see Contraindications (4), Warnings and Precautions (5.1, 5.3)]. The mean exposure to drospirenone (DRSP) in females with moderate liver impairment is approximately three times higher than the exposure in females with normal liver function. NEXTSTELLIS has not been studied in females with severe hepatic impairment [see Clinical Pharmacology (12.3)].

8.7 Renal Impairment

NEXTSTELLIS is contraindicated in females with renal impairment [see Contraindications (4), Warnings and Precautions (5.1)].

In subjects with creatinine clearance (CLcr) of 50–79 mL/min, serum DRSP levels were comparable to those in a control group with CLcr ≥ 80 mL/min. In subjects with CLcr of 30–49 mL/min, serum DRSP concentrations were on average 37% higher than those in the control group. In addition, there is a potential to develop hyperkalemia in subjects with renal impairment whose serum potassium is in the upper reference range, and who are concomitantly using potassium sparing drugs [see Warnings and Precautions (5.2), Drug Interactions (7.2) and Clinical Pharmacology (12.3)].

8.8 Race/Ethnicity

No clinically significant difference was observed between the pharmacokinetics of E4 or DRSP depending on race [see Clinical Pharmacology (12.3)].

8.9 Body Mass Index (BMI)/Body Weight

The safety and efficacy of NEXTSTELLIS in females with a BMI ≥ 35 kg/m^2 have not been adequately evaluated.

10 OVERDOSAGE

Overdosage of CHCs may cause nausea, vomiting, and severe headaches. Individual reports of thromboembolic complications and vaginal bleeding have occurred from overdosage. Pediatric patients with unintended CHC ingestion have reported nausea and vomiting and some developed irritability and drowsiness; rare reports described vaginal bleeding.

Overdosage Management Recommendations

Consider short-term prophylactic anticoagulation therapy for patients with high risk of VTE. Monitor serum potassium and sodium levels, and for evidence of metabolic acidosis.

11 DESCRIPTION

NEXTSTELLIS® (drospirenone and estetrol tablets) is an oral contraceptive. It is supplied in a transparent PVC/aluminum blister card containing 28 tablets:

- 24 pink active tablets contain 3 mg drospirenone and 14.2 mg of estetrol on the anhydrous basis. Drospirenone is a synthetic progestin and estetrol is a synthetic estrogen.
- 4 white inert tablets.

The chemical name for estetrol is estra-1,3,5(10)-triene-3,15α,16α,17α-tetrol monohydrate. It has a molecular formula of C18H24O4∙H2O and a molecular weight of 322.4 g/mol, equivalent to 304.4 g/mol (anhydrous). Estetrol has the following chemical structure:

Estetrol (monohydrate) is a white to off-white crystalline solid that is poorly soluble in water and aqueous solutions. It is soluble in methanol, ethanol, sparingly soluble in acetone, and slightly soluble in ethyl acetate and acetonitrile.

Drospirenone is chemically described as (6R,7R,8R,9S,10R,13S,14S,15S,16S,17S)-1,3',4',6,6a,7,8,9,10,11,12,13,14,15,15a,16-hexadecahydro10,13-dimethylspiro-[17H-dicyclopropa-[6,7:15,16]cyclopenta[a]phenanthrene-17,2'(5H)-furan]-3,5'(2H)-dione). It has a molecular weight of 366.5 g/mol, a molecular formula of C24H30O3, and the structural formula below:

Drospirenone is a white to almost white or slightly yellow crystalline powder. It is a neutral molecule with slight solubility in water.

The active tablet is a 6 mm, round pink film-coated tablet which contains 3 mg of drospirenone and 15 mg of estetrol as the monohydrate, equivalent to 14.2 mg of estetrol on the anhydrous basis, and the following inactive ingredients: corn starch, lactose monohydrate, magnesium stearate, povidone, and sodium starch glycolate. Each tablet is embossed on one side with a drop-shaped logo. The pink film-coating has the following inactive ingredients: hydrogenated cottonseed oil, hydroxypropyl cellulose, hypromellose, iron oxide red, talc, and titanium dioxide.

The inert tablet is a 6 mm, round white film-coated tablet which contains the inactive ingredients corn starch, lactose monohydrate, and magnesium stearate. Each tablet is embossed on one side with a drop-shaped logo. The film-coating has the following inactive ingredients: hydrogenated cottonseed oil, hydroxypropyl cellulose, hypromellose, talc, and titanium dioxide.

12 CLINICAL PHARMACOLOGY

12.1 Mechanism of Action

CHCs prevent pregnancy primarily by suppressing ovulation.

12.2 Pharmacodynamics

Drospirenone is a spironolactone analogue with anti-mineralocorticoid and antiandrogenic activity. The estrogen in NEXTSTELLIS is estetrol, a synthetic analogue of a native estrogen present during pregnancy, that is selective for nuclear estrogen receptor-α (ER-α) and ER-β.

Effect of NEXTSTELLIS on ovarian function

A clinical study evaluated the effect of NEXTSTELLIS on the suppression of ovarian activity as assessed by measurement of follicle size via transvaginal ultrasound and serum hormone (progesterone and estradiol) analyses in two of the three treatment cycles (24-day active tablet period plus 4-day pill-free period). No ovulations were observed during the study.

Cardiac Electrophysiology

At a dose 5 times the maximum recommended dose (i.e., supra-therapeutic dose of 15 mg DRSP /71 mg E4), NEXTSTELLIS does not prolong the QT interval to any clinically relevant extent.

Drugs That Have the Potential to Increase Serum Potassium Concentration

There is a potential for an increase in serum potassium concentration in females taking NEXTSTELLIS with other drugs that may increase serum potassium concentration [see Warnings and Precautions (5.2)].

A drug-drug interaction study of DRSP 3 mg /E2 1 mg versus placebo was performed in 24 mildly hypertensive postmenopausal females taking enalapril maleate 10 mg twice daily. Potassium concentrations were obtained every other day for a total of 2 weeks in all subjects. Mean serum potassium concentrations in DRSP/E2 treatment group relative to baseline were 0.22 mEq/L higher than those in the placebo group. Serum potassium concentrations also were measured at multiple time points over 24 hours at baseline and on Day 14. On Day 14, the ratios for serum potassium Cmax and AUC in the DRSP/E2 group to those in the placebo group were 0.955 (90% CI: 0.914, 0.999) and 1.010 (90% CI: 0.944, 1.08), respectively. No patient in either treatment group developed hyperkalemia (serum potassium concentrations > 5.5 mEq/L).

Other PD effects of NEXTSTELLIS

Table 7 displays pharmacodynamic effects of CHCs on hemostatic, metabolic, and endocrine parameters.

Table 7: Pharmacodynamics Effects of CHCs on Hemostatic, Metabolic, and Endocrine Parameters
Category | Direction of Change
Category | Increase | Decrease | No change
Coagulation Factors | ↑ Platelet count; factors II, VII antigen, VIII coagulant activity, IX, X, XII, VII-X complex, and beta-thromboglobulin; fibrinogen and fibrinogen activity; plasminogen antigen and activity | ↓(Accelerated) Prothrombin time, partial thromboplastin time, and platelet aggregation time ↓ Anti-factor Xa and antithrombin III, antithrombin III activity
Corticosteroids | ↑ Corticosteroid-binding globulin (CBG), total circulating corticosteroids | - | -
Glucose | - | ↓ Glucose tolerance | -
Lipids | ↑ | ↓ Low-density lipoprotein concentration | Plasma high-density lipoprotein (HDL) and HDL2 cholesterol subfraction concentration, triglyceride levels
Mineralocorticoids | ↑ Aldosterone
Plasma proteins | ↑ Concentrations of angiotensinogen/renin substrate, alpha-1 antitrypsin, ceruloplasmin | - | -
Sex hormones | ↑ Sex hormone-binding globulin (SHBG) | ↓ Possible decreased free testosterone concentrations ↓ Androstenedione, progesterone, free testosterone, estradiol | DHEA-S, FSH, LH,Dihydrotestosterone
Thyroid hormones | ↑ Thyroxin-binding globulin (TBG), total thyroid hormone levels, total T4 and T3 levels | ↓ T3 resin uptake | ↔ TSH, Free T4 and free T3 concentrations in females with normal thyroid function

12.3 Pharmacokinetics

Absorption, Distribution, Metabolism, and Excretion

The pharmacokinetic properties of E4 and DRSP following administration of NEXTSTELLIS are provided in TABLE 8.

Table 8. Pharmacokinetics of E4 and DRSP
 | E4 | DRSP
Multiple-dose pharmacokinetics parameters
Mean (CV%) Cmax, ng/mL | 17.9 (68.1) | 48.7 (24.6)
Mean (CV%) AUC0-24h, ng*hr/mL | 59.1 (24.3) | 519.0 (27.7)
Dose Proportionality | 15 mg to 75 mg | 1-10 mg
Time to Steady State, days | 4 | 10
Accumulation Ratio | 1.6 | 2.3
Absorption
Median (range) Tmax, hours | 0.5 (0.5 to 2) | 1.0 (1.0 to 3.0)
Effect of high-fat meal (relative to fasting)
Geometric Mean (90% CI) Cmax, Ratio | 0.51 (0.37, 0.70) | 0.75 (0.66, 0.84)
Geometric Mean (90% CI) AUC0-INF, Ratio | 1.01 (0.86, 1.19) | 1.08 (1.02, 1.14)
Distribution
Plasma Protein Binding | 46% to 50% | 95% to 97% [Bound primarily to albumin]
Elimination
Elimination Half-life, hours | 27 [Undergoes enterohepatic recycling] | 34
Metabolism
Primary Pathways | Phase 2 metabolism to form glucuronide and sulphate conjugates which have negligible in-vitro estrogenic activity. In vitro studies show that UGT2B7 is the dominant UGT isoform that catalyzes the formation of E4-16-glucuronide | CYP3A4; two main metabolites: acid form of DRSP generated by opening of lactone ring and the 4,5-dihydrodrospirenone formed by reduction followed by sulfation. Both metabolites are not pharmacologically active.
Excretion
Primary Pathways
% Dose in Urine | 69% (0% unchanged) | 38%
% Dose in Feces | 22% (100% unchanged) | 44%
Cmax= Maximum plasma concentration; AUC0-t= Area under the plasma concentration-time curve integrated from time of administration (0) to time of last quantifiable observation (t); AUC0-INF= Area under the plasma concentration-time curve from time of administration extrapolated to infinity from AUC0-t; CI= Confidence interval; Tmax= Time to maximum concentration

Specific Populations

No clinically significant differences in the pharmacokinetics of E4 or DRSP in females were observed based on race/ethnicity (Japanese and Caucasian).

Patients with Hepatic Impairment

The effect of hepatic impairment on the pharmacokinetics of E4 is unknown.

The mean exposure to DRSP is approximately three times higher in females with moderate liver impairment than the exposure in females with normal liver function. The effect of severe hepatic impairment on the pharmacokinetics of DRSP is unknown.

Patients with Renal Impairment

The effect of renal impairment on the pharmacokinetics of E4 is unknown. The mean serum DRSP concentrations increased by 37% in subjects with CLcr of 30 to 49 mL/min on a low potassium diet using potassium-sparing drugs. No clinically significant differences in the pharmacokinetics of DRSP were observed based on CLcr of 50 to 79 mL/min. DRSP treatment did not show any clinically significant effect on serum potassium concentration. Although hyperkalemia was not observed in the study, in five of the seven subjects who continued use of potassium-sparing drugs during the study, mean serum potassium concentrations increased by up to 0.33 mEq/L.

Drug Interaction Studies

Clinical Studies

Strong CYP3A4 Inhibitor: Concomitant use of a COC containing DRSP 3 mg/EE 20 µg with ketoconazole (strong CYP3A4 inhibitor) increased the AUC0-24h and Cmax of DRSP by 2.68-fold (90% CI: 2.44, 2.95) and 1.97-fold (90% CI: 1.79, 2.17), respectively.

CYP3A4 Inducer: Concomitant use of a COC containing DRSP 3 mg/EE 20 µg with high dose (strong CYP3A induction) and low dose of rifampin (weak CYP3A4 induction) decreased the AUC0-24h of DRSP by 86% (90% CI: 85%, 87%) and 30% (90% CI: 25%, 34%), respectively.

UGT2B7 Inhibitor: No clinically significant differences in the pharmacokinetics of NEXTSTELLIS were observed when used concomitantly with valproic acid (UGT2B7 inhibitor).

CYP3A Substrate: Pharmacokinetics of CYP3A substrates midazolam and simvastatin were not influenced by steady state DRSP concentrations achieved after administration of 3 mg DRSP/day.

CYP2C19 Substrate: Daily oral administration of 3 mg DRSP for 14 days did not affect the oral clearance of the CYP2C19 substrate omeprazole (40 mg, single oral dose) and the CYP2C19 product 5-hydroxy omeprazole.

In Vitro Studies

E4 is not a substrate of CYP1A1, CYP2B6, CYP2C8, CYP2C9, CYP2D6, CYP3A4, OATP1B1, OATP1B3, OAT1, OAT3, OCT2, MATE1, MATE2-K. E4 is unlikely to induce CYP1A2, CYP2B6, CYP3A4 or inhibit CYP3A4, CYP1A2, CYP2B6, CYP2C8, CYP2C9, CYP2C19, CYP2D6, CYP2E1, UGT1A9, UGT2B7, drug transporters P-pg, BCRP, OATP1B1, OATP1B3, OAT1, OAT3, OCT2, MATE1 and MATE2-K or at clinically relevant dose.

Effects of NEXTSTELLIS on Lamotrigine

Estrogens are known to decrease plasma concentrations of lamotrigine, likely due to induction of lamotrigine glucuronidation. No in vitro or in vivo data are available to determine the impact of E4 on lamotrigine exposure.

13 NONCLINICAL TOXICOLOGY

13.1 Carcinogenesis, Mutagenesis, Impairment of Fertility

In a 24-month oral carcinogenicity study in mice with doses up to 10 mg/kg/day DRSP, equating to 2 times the maximum clinical exposure (based on AUC), there was an increase in carcinomas of the harderian gland in the high dose DRSP group. In a similar study in rats given doses up to 10 mg/kg/day DRSP, 10 times the maximum clinical exposure (based on AUC), there was an increased incidence of benign and total (benign and malignant) adrenal gland pheochromocytomas in the high dose DRSP group.

Mutagenesis studies for DRSP were conducted in vivo and in vitro and no evidence of mutagenic activity was observed. E4 is not considered to be genotoxic based on weight of evidence from in vivo and in vitro mutagenesis studies.

14 CLINICAL STUDIES

Pregnancy Prevention

The efficacy of NEXTSTELLIS was evaluated in a prospective, multicenter, open-label, single-arm study in North America (NCT02817841; C302) of one-year duration that enrolled 1,674 females 16 to 35 years of age. The mean age was 25.8 years and mean BMI was 25.8 kg/m^2. Females with a BMI between 30 and 35 kg/m^2 accounted for 22.3% of the study population. Females with a BMI greater than 35 kg/m^2 were not enrolled in the study. The racial distribution was 70.1% Caucasian, 19.5% Black or African American, 4.8% Asian, 0.9% American Indian or Alaska native, 0.4% Native Hawaiian or other Pacific Islander and 4.2% other.

A total of 26 on-treatment pregnancies occurred in 1,524 females contributing 12,763 at-risk cycles. The overall Pearl Index was 2.65 (95% CI: 1.73-3.88) per 100 woman-years of use. Table 9 lists the Pearl Index by BMI subgroup. A trend of decreasing effectiveness with increasing BMI was observed in the study.

Table 9 Pearl Index Based on At-Risk Cycles and Reported Pregnancies in Females ≤ 35 Years of Age in Study C302
Subgroup | N [N = all females aged 16-35 with at least 1 at-risk cycle.] | On-treatment pregnancies | At-risk cycles | Pearl Index (95% CI)
Study C302 | 1524 | 26 | 12,763 | 2.65 (1.73, 3.88)
BMI (kg/m^2)
< 30 | 1,187 | 20 | 10,113 | 2.57 (1.57, 3.97)
≥ 30 to < 35 [One female with a BMI of 48 kg/m^2 was enrolled and included in the efficacy analysis.] | 337 | 6 | 2,650 | 2.94 (1.08, 6.41)

16 HOW SUPPLIED/STORAGE AND HANDLING

16.1 How Supplied

NEXTSTELLIS® (drospirenone and estetrol tablets) is available in a blister card, with 28 6-mm round, bi-convex film-coated tablets in the following order:

- 24 pink active film-coated tablets containing 3 mg drospirenone and 14.2 mg estetrol embossed with a drop-shaped logo on one side.
- 4 white inert film-coated tablets embossed with a drop-shaped logo on one side.

NEXTSTELLIS® is supplied in cartons containing 1 blister card of 28 tablets: NDC 51862-258-01.

16.2 Storage

Store at 20°C to 25°C (68°F to 77°F), excursions permitted to 15°C to 30°C (59°F to 86°F) [see USP Controlled Room Temperature].

16.3 Disposal

Dispose unused medication via a take-back option if available. Otherwise, follow FDA instructions for disposing medication in the household trash, www.fda.gov/drugdisposal. Do NOT flush down the toilet.

17 PATIENT COUNSELING INFORMATION

Advise the patient to read the FDA-Approved patient labeling (Patient Information and Instructions of Use).

Sexually Transmitted Infections

Advise females that NEXTSTELLIS does not protect against HIV infection or other sexually transmitted infections.

Important Administration Instructions and Instructions for Missed Doses

Instruct females to take one tablet daily by mouth at the same time every day. Advise patients about what to do in the event that pills are missed [see Dosage and Administration (2.3)].

- Advise females starting NEXTSTELLIS to use additional nonhormonal contraception for 7 days after the first dose unless NEXTSTELLIS is started on the first day (Day 1) of menses [see Dosage and Administration (2.1)]
- Advise females who miss more than two consecutive days of NEXTSTELLIS or experience vomiting or diarrhea for > 48 hours consecutively to use additional nonhormonal contraception for 7 days [see Dosage and Administration (2.3, 2.4)]

Thromboembolic Disorders and Other Vascular Problems [see Warnings and Precautions (5.1)].

- Advise females that there is an increased risk of arterial and/or venous thrombotic/thromboembolic events with NEXTSTELLIS and the risk of arterial and/or venous thrombotic/thromboembolism is greater in smokers and females with preexisting medical conditions including hypertension, dyslipidemia, diabetes, and obesity.
- Advise patients of the pertinent factors that further increase their risk and ways to diminish the risk, e.g., to stop smoking (if applicable).
- Advise patients to contact their healthcare professional for any signs or symptoms of arterial and/or VTE
- Advise patients to contact their healthcare professional if they will be immobilized for a prolonged period of time.

Hyperkalemia

Advise females to contact their healthcare professional if signs or symptoms of hyperkalemia develop [see Warnings and Precautions (5.2)].

Hypertension

Advise females that NEXTSTELLIS can cause an increase in blood pressure over time. Instruct patients to contact their healthcare professional if blood pressure increases [see Warnings and Precautions (5.3)].

Liver Disease

Advise females that use of NEXTSTELLIS can cause elevated liver enzymes and can increase the risk of liver tumors. Instruct females to contact their healthcare professional for any signs or symptoms of liver disease [see Warnings and Precautions (5.5)].

Glucose Tolerance

Advise females that NEXTSTELLIS may decrease glucose tolerance. Instruct females with diabetes and prediabetes to contact their healthcare professional for any signs or symptoms of hyperglycemia [see Warnings and Precautions (5.7) and Clinical Pharmacology (12.2)].

Gallbladder Disease and Cholestasis

Advise females that use of NEXTSTELLIS is associated with an increased risk of developing and/or worsening gallbladder disease. Instruct patients to contact their healthcare professional for any signs or symptoms of gallbladder disease [see Warnings and Precautions (5.8)].

Bleeding Irregularities, Amenorrhea, and Pregnancy

Advise females that NEXTSTELLIS can cause unscheduled bleeding and spotting, as well as amenorrhea and oligomenorrhea. Advise females to contact their health care professional if amenorrhea occurs in two or more consecutive cycles or symptoms of pregnancy occur, e.g., morning sickness or unusual breast tenderness. Instruct females to stop NEXTSTELLIS if pregnancy is confirmed during use [see Warnings and Precautions (5.11) and Use in Specific Populations (8.1)].

Chloasma

Advise females that NEXTSTELLIS can cause chloasma and the risk is highest in females with a history of chloasma, especially chloasma gravidarum. Instruct females to take precautions to limit UVA and UVB exposure while using NEXTSTELLIS [see Warnings and Precautions (5.14)].

Lactation

Advise postpartum females that NEXTSTELLIS may reduce breast milk production. Advise females that this reduction is less likely to occur if breast-feeding is well established [see Use in Specific Populations (8.2)].

Drug Interactions

NEXTSTELLIS may interact with many drugs, foods, and dietary supplements. Therefore, advise females to report to their healthcare professional the use of any other prescription or nonprescription drugs or dietary supplements [see Drug Interactions (7.1, 7.2)].

Distributed by:
Mayne Pharma
Raleigh, NC 27609

PATIENT INFORMATION
NEXTSTELLIS® (NEXT ste LIS)
(drospirenone and estetrol tablets)
for oral use

What is the most important information I should know about NEXTSTELLIS?
Do not use NEXTSTELLIS if you smoke cigarettes and are over 35 years old. Smoking increases your risk of serious cardiovascular side effects (heart and blood vessel problems) from birth control pills, including death from heart attack, blood clots or stroke. The risk increases with age and the number of cigarettes you smoke.

What is NEXTSTELLIS?

- NEXTSTELLIS is a birth control pill (oral contraceptive) used by females to prevent pregnancy.
- NEXTSTELLIS does not protect against HIV infections (AIDS) and other sexually transmitted infections.
- NEXTSTELLIS may be less effective if you have a body mass index (BMI) of 30 or higher. In females with a BMI of 30 or higher, NEXTSTELLIS may become less effective as your BMI increases.
- It is not known if NEXTSTELLIS is safe and effective in females with a BMI of 35 or higher.

How does NEXTSTELLIS work for contraception?
Your chance of getting pregnant depends on how well you follow the directions for taking your birth control pills. The better you follow the directions, the less chance you have of getting pregnant.
Based on the results of one clinical study of a regimen of drospirenone 3 mg and estetrol 14.2 mg tablets, about 2 out of 100 females may get pregnant within the first year they use NEXTSTELLIS.
The following chart shows the chance of getting pregnant for females who use different methods of birth control. Each box on the chart contains a list of birth control methods that are similar in effectiveness. The most effective methods are at the top of the chart. The box on the bottom of the chart shows the chance of getting pregnant for females who do not use birth control and are trying to get pregnant.

Do not take NEXTSTELLIS if you:

- smoke and are 35 years of age and older.
- have or have had blood clots in your arms, legs, lungs, or eyes.
- have a problem with your blood that makes it clot more than normal.
- have certain heart valve problems or an irregular heart beat that increases your risk of having blood clots.
- had a stroke.
- had a heart attack.
- have high blood pressure that cannot be controlled by medicine or have high blood pressure with blood vessel problems.
- have diabetes:
  - with high blood pressure or kidney, eye, nerve, or blood vessel damage, or
  - for more than 20 years.
- have certain kinds of severe migraine headaches with aura.
- have liver problems, including liver tumors.
- have any unexplained vaginal bleeding.
- have or have had breast cancer or any cancer that is sensitive to female hormones.
- have kidney disease or kidney failure.
- have reduced adrenal gland function (adrenal insufficiency).
- take any Hepatitis C drug combination containing ombitasvir/paritaprevir/ritonavir, with or without dasabuvir. This may increase levels of the liver enzyme "alanine aminotransferase" (ALT) in the blood.

If any of these conditions happen while you are taking NEXTSTELLIS, stop taking NEXTSTELLIS right away and talk to your healthcare provider. Use non-hormonal contraception when you stop taking NEXTSTELLIS.

Before taking NEXTSTELLIS, tell your healthcare provider about all of your medical conditions, including if you:

- are scheduled for surgery. NEXTSTELLIS may increase your risk of blood clots after surgery. Talk to your healthcare provider about taking NEXTSTELLIS before and after your surgery or if you are going to be unable to walk for an extended period of time (immobilized).
- are depressed now or have been depressed in the past.
- had yellowing of your skin or eyes (jaundice) caused by pregnancy (cholestasis of pregnancy).
- are pregnant or think you may be pregnant.
- are breastfeeding or plan to breastfeed. NEXTSTELLIS may decrease the amount of breast milk you make. NEXTSTELLIS may pass into your breast milk. Talk to your healthcare provider about the best birth control method for you while breastfeeding.

Tell your healthcare provider about all the medicines you take, including prescription and over-the-counter medicines, vitamins, and herbal supplements. If you are currently on daily, long-term treatment for a chronic condition with any of the following medicines, you should talk to your healthcare provider before taking NEXTSTELLIS:

- CYP inducers (aprepitant, barbiturates, bosentan, carbamazepine, efavirenz, felbamate, griseofluvin, oxycarbazepine, phenytoin, rifampin, rifabutin, topiramate, products containing St. John's wort, and others)
- CYP inhibitors (itraconazole, voriconazole, fluconazole, ketoconazole and others)
- HIV/hepatitis C virus protease inhibitors and non-nucleoside reverse transcriptase inhibitors (nelfinavir, ritonavir, boceprevir, telaprevir, indinavir, nevirapine, etravirine and others)
- Lamotrigine
- Potassium-sparing diuretics (spironolactone and others)
- Potassium supplementation
- Corticosteroids

NEXTSTELLIS may affect the way other medicines work, and other medicines may affect how well NEXTSTELLIS works.
Know the medicines you take. Keep a list of them to show your healthcare provider and pharmacist when you get a new medicine.

How should I take NEXTSTELLIS?

- Read the detailed Instructions for Use at the end of this Patient Information leaflet about the right way to take your NEXTSTELLIS.

What are the possible side effects of NEXTSTELLIS?

- NEXTSTELLIS may cause serious side effects including blood clots in your lungs, heart attack, or a stroke that may lead to death. Some other examples of serious blood clots include blood clots in the legs or eyes. Serious blood clots can happen especially if you smoke, are obese, have high blood pressure, have diabetes, have high cholesterol, or are older than 35 years of age. Serious blood clots are more likely to happen when you:
  - first start taking birth control pills
  - restart the same or different birth control pills after not using them for a month or more
  Call your healthcare provider or go to a hospital emergency room right away if you have:
  - leg pain that will not go away
  - sudden severe shortness of breath
  - sudden change in vision or blindness
  - chest pain
  - a sudden, severe headache unlike your usual headaches
  - weakness or numbness in your arm or leg
  - trouble speaking

Other serious side effects include:

- high potassium levels in your blood (hyperkalemia). Certain medicines and conditions can also increase the potassium levels in your blood. Your healthcare provider may check the potassium levels in your blood during treatment with NEXTSTELLIS. Call your healthcare provider or go to a hospital emergency room right away if you have signs or symptoms of high potassium levels in your blood including:
  - weakness or numbness in an arm or leg
  - palpitations (feel like your heart is racing or fluttering) or irregular heartbeat
  - nausea
  - vomiting
  - severe pain in your chest
  - shortness of breath
- high blood pressure. You should see your healthcare provider to check your blood pressure regularly.
- new or worsening headaches including migraine headaches.
- possible cancer that is sensitive to female hormones, such as breast cancer, skin cancer (melanoma), lung cancer, and brain cancer.
- liver problems, including:
  - an increase in liver enzymes in the blood
  - rare liver tumors
  - jaundice. Call your healthcare provider if you have yellowing of your skin or eyes.
- changes in the sugar and fat (cholesterol and triglycerides) levels in your blood.
- gallbladder problems (cholestasis), especially if you previously had cholestasis of pregnancy.
- irregular or unusual vaginal bleeding or spotting between your menstrual periods, especially during the first 4 months of taking NEXTSTELLIS, or the absence of menstrual periods.
- Depression.
- possible cancer in your cervix.
- swelling of your skin especially around your mouth, eyes, and in your throat (angioedema). Call your healthcare provider right away if you have a swollen face, lips, mouth, tongue or throat, which may lead to difficulty swallowing or breathing. Your chance of having angioedema is higher if you have a history of angioedema.
- dark patches of skin around your forehead, nose, cheeks and around your mouth, especially during pregnancy (chloasma). Females who tend to get chloasma should avoid spending a long time in sunlight, tanning booths, and under sun lamps while taking NEXTSTELLIS. Use sunscreen if you have to be in the sunlight.

What are the most common side effects of NEXTSTELLIS?
The most common side effects of NEXTSTELLIS include:

- irregular vaginal bleeding (including absence of period)
- mood changes
- headache
- breast tenderness, pain, and discomfort

- pain with your periods
- acne
- weight gain
- decreased sex drive

These are not all of the possible side effects of NEXTSTELLIS.
Call your doctor for medical advice about side effects. You may report side effects to FDA at 1-800-FDA-1088.

Do birth control pills cause cancer?
It is not known if hormonal birth control pills cause breast cancer. Some studies, but not all, suggest that there could be a slight increase in the risk of breast cancer among current users with longer duration of use.
If you have breast cancer now, or have had it in the past, do not use hormonal birth control because some breast cancers are sensitive to hormones.
Females who use birth control pills may have a slightly higher chance of getting cervical cancer. However, this may be due to other reasons such as having more sexual partners.

What if I want to become pregnant?
You may stop taking the pill whenever you wish. Consider a visit with your healthcare provider for a pre-pregnancy checkup before you stop taking the pill.

What should I know about my period when taking NEXTSTELLIS?
Irregular vaginal bleeding or spotting may happen while you are taking NEXTSTELLIS, especially during the first 4 months of use. If the irregular vaginal bleeding or spotting continues or happens again after you have had regular menstrual cycles, call your healthcare provider. It is important to continue taking your pills on a regular schedule to prevent a pregnancy.

What if I miss my scheduled period when taking NEXTSTELLIS?
Some females miss periods on hormonal birth control, even when they are not pregnant. However, if you go 2 or more months in a row without a period, or you miss your period after a month where you did not take all of your NEXTSTELLIS correctly, call you healthcare provider because you may be pregnant. Also call your healthcare provider if you have symptoms of pregnancy such as morning sickness or unusual breast tenderness. Stop taking NEXTSTELLIS if you are pregnant.

What else should I know about taking NEXTSTELLIS?

- If you are scheduled for any lab tests, tell your healthcare provider you are taking NEXTSTELLIS. Certain blood tests may be affected by NEXTSTELLIS.

How should I store NEXTSTELLIS?

- Store NEXTSTELLIS at room temperature between 68°F to 77°F (20°C to 25°C).
- Throw away unused NEXTSTELLIS through a take-back option, if available. You may also visit www.fda.gov/drugdisposal for FDA instructions for throwing away medicine in your household trash. Do not flush NEXTSTELLIS down the toilet.
- Keep NEXTSTELLIS and all medicines out of the reach of children.

General information about the safe and effective use of NEXTSTELLIS.
Medicines are sometimes prescribed for purposes other than those listed in a Patient Information leaflet. Do not use NEXTSTELLIS for a condition for which it was not prescribed. Do not give NEXTSTELLIS to other people, even if they have the same symptoms that you have. It may harm them.
You can ask your pharmacist or healthcare provider for information about NEXTSTELLIS that is written for health professionals.

What are the ingredients in NEXTSTELLIS?
Active ingredient: Pink tablets: drospirenone and estetrol
Inactive ingredients:

- Pink tablets: corn starch, lactose monohydrate, magnesium stearate, povidone, and sodium starch glycolate. Film-coating: hydrogenated cottonseed oil, hydroxypropyl cellulose, hypromellose, iron oxide red, talc, and titanium dioxide.
- White tablets: corn starch, lactose monohydrate, and magnesium stearate. Film coating: hydrogenated cottonseed oil, hydroxypropyl cellulose, hypromellose, talc, and titanium dioxide.

For more information, go to www.maynepharma.com or call 1-844-825-8500

INSTRUCTIONS FOR USE

NEXTSTELLIS® (NEXT ste LIS)
(drospirenone and estetrol tablets)
for oral use

Important Information about taking NEXTSTELLIS

- Take 1 pill every day at the same time. Take the pills in the order directed on your blister pack.
- Swallow both the pink pills and white pills whole. You may take NEXTSTELLIS with or without food.
- Do not skip your pills, even if you do not have sex often. If you miss pills (including starting the pack late) you could get pregnant. The more pills you miss, the more likely you are to get pregnant.
- If you have trouble remembering to take NEXTSTELLIS, talk to your healthcare provider. When you first start taking NEXTSTELLIS, spotting or light bleeding in between your periods may occur. Contact your healthcare provider if this does not go away after a few months.
- Some females miss periods on hormonal birth control, even when they are not pregnant. However, if you miss a period and have not taken NEXTSTELLIS according to the directions, or miss 2 periods in a row, or feel like you may be pregnant, call your healthcare provider. If you have a positive pregnancy test, you should stop taking NEXTSTELLIS.
- If you have vomiting or diarrhea (within 3 to 4 hours after you take a pink active pill), take a new pink active pill that was scheduled for the next day as soon as possible. If possible, take the new pink active pill within 12 hours of the time you usually take it. If you miss more than 2 pink active pills, follow the instructions for "What Should I do if I miss any NEXTSTELLIS pills?"
- If you have vomiting or diarrhea for more than 2 days (48 hours) in a row, or if you take certain medicines, including some antibiotics and some herbal products such as St. John's Wort, your pills may not work as well. Use an additional non-hormonal birth control method, such as condoms or spermicide, until you talk to your healthcare provider.
- Talk to your healthcare provider before you have major surgery. Be sure to use another form of non-hormonal birth control (such as condoms or spermicide) if your healthcare provider tells you to stop NEXTSTELLIS before your surgery.

Before you start taking NEXTSTELLIS

- Decide what time of day you want to take your pill. It is important to take it at the same time every day and in the order as directed on your blister pack.
- Have backup non-hormonal birth control (such as condoms or spermicide) available and an extra full pack of pills if possible.

When should I start taking NEXTSTELLIS?

If you start taking NEXTSTELLIS and you have not used a hormonal birth control method before:

- Start on the first day (Day 1) of your natural menstrual period (Day 1 Start).

You do not need a back-up non-hormonal birth control method.

- If you start taking NEXTSTELLIS on any day other than the first day of your natural menstrual period, use a back-up non-hormonal birth control method (such as condoms or spermicide) until you have taken one (1) active (pink) pill every day for seven (7) days.

If you start taking NEXTSTELLIS and you are switching from another birth control pill:

- Start your new NEXTSTELLIS pack on the same day that you would start the next pack of your previous birth control method.
- Do not continue taking the pills from your previous birth control pack.

If you start taking NEXTSTELLIS and previously used a vaginal ring or transdermal patch:

- Start using NEXTSTELLIS on the day you would have reapplied the patch or inserted the vaginal ring.

If you start taking NEXTSTELLIS and you are switching from a progestin-only method such as an implant or injection:

- Start taking NEXTSTELLIS on the day of removal of your implant or on the day when you would have had your next injection.

If you start taking NEXTSTELLIS and you are switching from an intrauterine device or system (IUD or IUS):

- Start taking NEXTSTELLIS on the day of removal of your IUD or IUS.
- You do not need a non-hormonal back-up birth control method if your IUD or IUS is removed on the first day (Day 1) of your period. If your IUD or IUS is removed on any other day, use a non-hormonal back-up birth control method such as condoms or spermicide for the first 7 days that you take NEXTSTELLIS.

If you start taking NEXTSTELLIS after you have given birth and you were more than 20 weeks pregnant:

- Do not start NEXTSTELLIS earlier than 4 weeks after you have given birth.
- If your menstrual cycles have returned, see "If you start taking NEXTSTELLIS and you have not used a hormonal birth control method before".
- If your menstrual cycles have not returned, use additional non-hormonal birth control (such as condoms or spermicide) for the first 7 days that you take NEXTSTELLIS.

If you start taking NEXTSTELLIS after an abortion or miscarriage and you were 14 weeks pregnant or less:

- If within the first 7 days of abortion or miscarriage:
  - Use additional non-hormonal birth control such as condoms or spermicide for the first 7 days you take NEXTSTELLIS.
- After the first 7 days following an abortion or miscarriage:
  - See "If you start taking NEXTSTELLIS and you have not used a hormonal birth control method before".

If you start taking NEXTSTELLIS after an abortion or miscarriage and you were more than 14 weeks pregnant but 20 weeks pregnant or less:

- Start NEXTSTELLIS after 4 weeks following the abortion or miscarriage.
- If your menstrual cycles have returned, see "If you start taking NEXTSTELLIS and you have not used a hormonal birth control method before".
- If your menstrual cycles have not returned, use additional non-hormonal birth control (such as condoms or spermicide) for the first 7 days you take NEXTSTELLIS.

Keep a calendar to track your menstrual period. If this is the first time you are taking birth control pills, read, "When should I start taking NEXTSTELLIS?" above and follow these instructions.

Before you start taking your pills

- Decide what time of day you want to take your pill. It is important to take it at about the same time every day.
- Look at your NEXTSTELLIS pill pack. See the Figure below. The pill pack has 24 "active" pink pills (with hormone) to take for 3 weeks and 3 days, followed by 4 "inactive" white pills (without hormone).

When to start the first pack of pills

Start on the first day (Day 1) of your natural menstrual period (Day 1 start). Pick a time of day which will be easy to remember.

Day 1 Start:

1. Pick the day label strip that starts with the first day of your period.
2. Place this day label strip on the pill dispenser over the area that says: "Place enclosed day label here".
3. Take the first active pink pill of the first pack during the first 24 hours of your period. Take 1 pill every day in the order of the blister pack, at the same time each day, for 28 days.
4. The day after taking the last pill on Day 28 from the blister pack, start taking the first pill from the new pack, on the same day of the week as the first pack. Take the first pill in the new pack whether or not you are having your period.

What should I do if I miss any NEXTSTELLIS pills?

If you miss 1 pink active pill in Weeks 1, 2 or 3, follow these steps:

- Take it as soon as you remember. Take the next pill at your regular time. This means you may take 2 pills in 1 day.
- Then continue taking 1 pill every day until you finish the pack.
- You do not need to use a back-up non-hormonal birth control method if you have sex.

If you miss 2 or more pink active pills in Week 1 or Week 2 of your pack, follow these steps:

- Take 1 missed pill as soon as possible and take the pill scheduled for the current day (which means you will take 2 pills in 1 day).
- Throw away the other missed pills.
- Then continue taking 1 pill a day until the pack is finished.
- Use a back-up non-hormonal birth control method (such as condoms or spermicide) if you have sex during the first 7 days after missing your pills.

If you miss 2 pink active pills in a row in week 3 of your pack, follow these steps:

- Take 1 missed pill as soon as possible and take the pill scheduled for the current day (which means you will take 2 pills in 1 day).
- Throw away the other missed pills.
- Continue taking 1 pill a day until you finish the pink active pills in the pack. Then throw away the inactive white pills in the pack.
- Start a new pack of pills the next day.
- If you miss your period this month, call your healthcare provider because you might be pregnant.
- You could become pregnant if you have sex during the first 7 days after you restart your pills. You should use a back-up non-hormonal birth control method (such as condoms or spermicide) if you have sex during the first 7 days after you restart your pills.

If you miss 1 or more white inactive pills, follow these steps:

- Skip the missed pill days.
- Continue taking 1 pill a day until the pack is finished.

If you have any questions or are unsure about the information in this leaflet, call your healthcare provider. They have a more technical leaflet called the Professional Labeling which you may read.

This Patient Information and Instructions for Use have been approved by the U.S. Food and Drug Administration.

Distributed by:
Mayne Pharma
Raleigh, NC 27609

Approved: 02/2023

PRINCIPAL DISPLAY PANEL - Kit Carton

NDC 51862-258-01

nextstellis®
(drospirenone and
estetrol tablets)
3 mg/14.2 mg

This product (like all oral contraceptives)
is intended to prevent pregnancy.
It does not protect against HIV infection
(AIDS) and other sexually transmitted
diseases.

Rx Only

1 Blister Card Containing 28 Tablets

mayne pharma